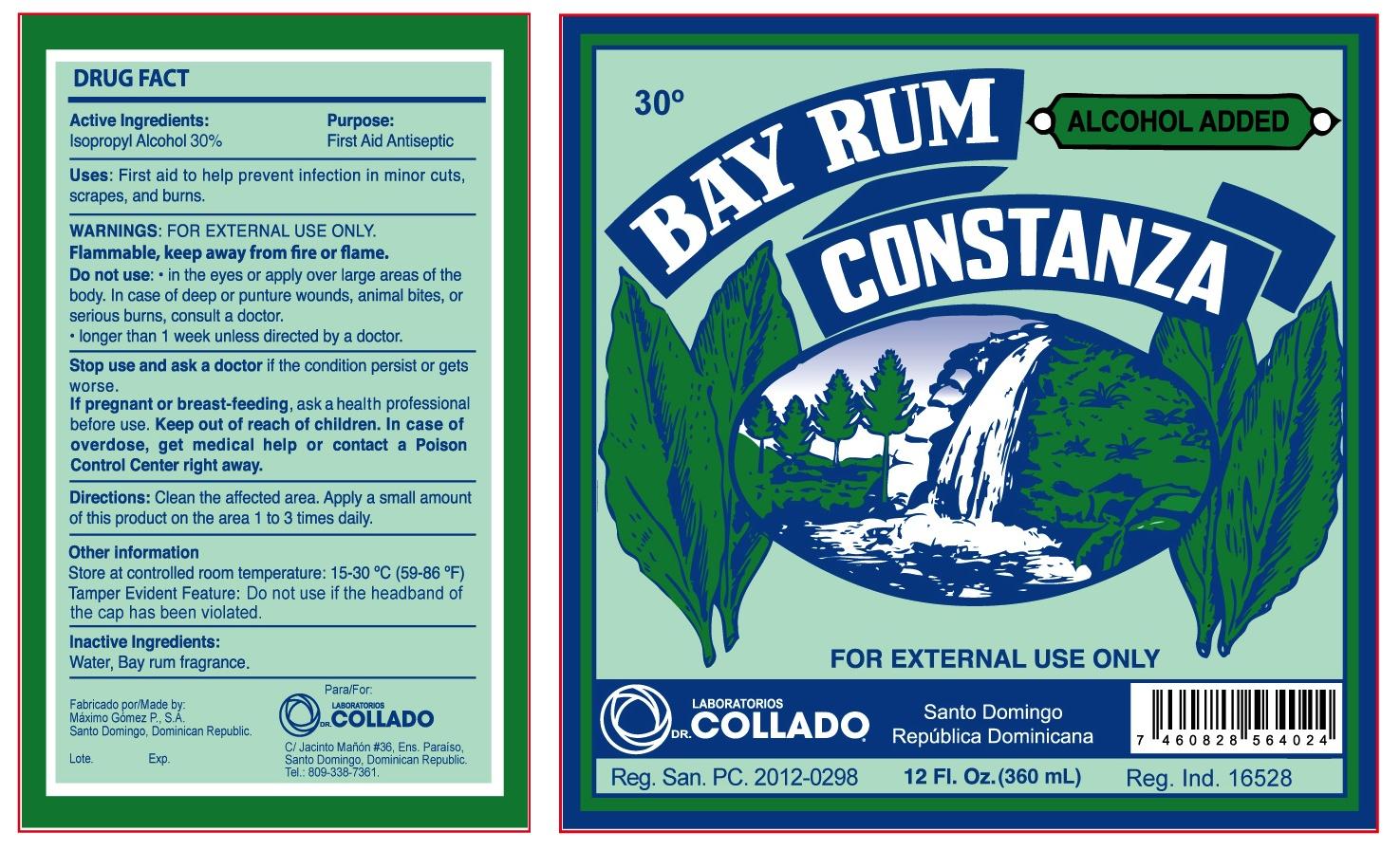 DRUG LABEL: Bay Rum Constanza
NDC: 42333-101 | Form: LIQUID
Manufacturer: Laboratorios Dr. Collado, C x A.
Category: otc | Type: HUMAN OTC DRUG LABEL
Date: 20130603

ACTIVE INGREDIENTS: ISOPROPYL ALCOHOL 30 mg/30 mL
INACTIVE INGREDIENTS: WATER

Drug Facts

Active Ingredients Purpose

Isopropyl Alcohol 30% First Aid Antiseptic

Purpose

First aid antiseptic

INDICATIONS AND USAGE

Uses:First aid to help prevent infection in minor cuts, scrapes, and burns.

Warnings:FOR EXTERNAL USE ONLY.

Flammable, keep away from fire or flame.

Stop use and ask a doctor if the condition persists or get worse.

Do not use:

- in the eyes or apply over large areas of the body. In case of deep or puncture wounds, animal bites or serious burns, consult a doctor.
- longer than 1 week unless directed by a doctor.

PREGNANCY OR BREAST FEEDING

If pregnant or breast-feeding,ask a health professional before use.

Keep out of reach of children. In case of overdose, get medical help or contact a Poison Control Center right away.

DOSAGE AND ADMINISTRATION

Directions:Clean the affected area. Apply a small amount of this product on the area 1 to 3 times daily.

Inactive ingredients:

Water, Bay rum fragrance.

QUESTIONS

Laboratorios Dr. Collado

809-338-7361